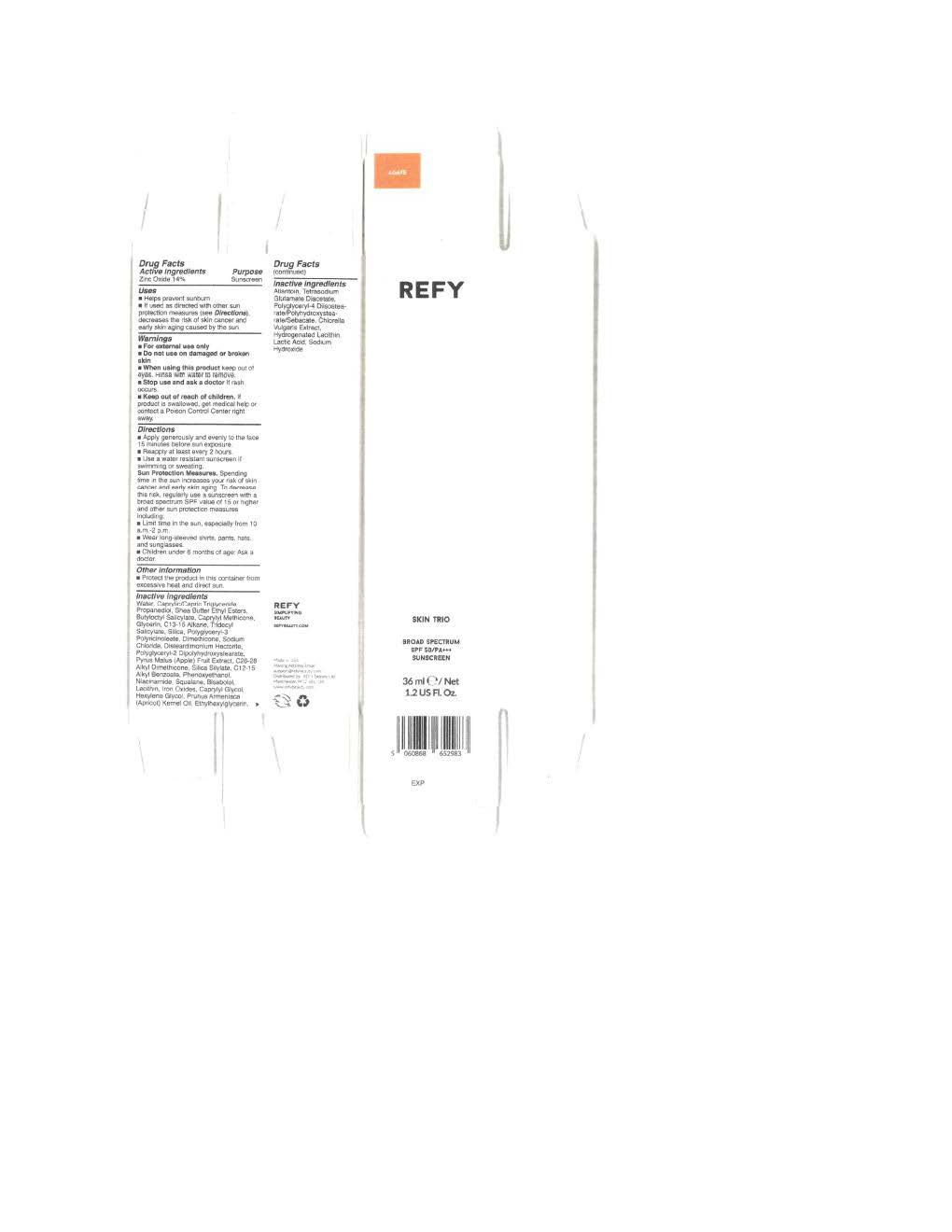 DRUG LABEL: Refy Skin Trio
NDC: 84047-2090 | Form: LOTION
Manufacturer: Refy
Category: otc | Type: HUMAN OTC DRUG LABEL
Date: 20251106

ACTIVE INGREDIENTS: ZINC OXIDE 154 mg/1 mL
INACTIVE INGREDIENTS: DIMETHICONE 1000; DISTEARDIMONIUM HECTORITE; FERRIC OXIDE RED; HEXYLENE GLYCOL; LACTIC ACID; NIACINAMIDE; C13-15 ALKANE; CHLORELLA VULGARIS; ALLANTOIN; SILICON DIOXIDE; CAPRYLYL GLYCOL; POLYGLYCERYL-2 DIPOLYHYDROXYSTEARATE; GLYCERIN; CAPRYLYL METHICONE; PRUNUS ARMENIACA (APRICOT) FRUIT; ETHYLHEXYLGLYCERIN; PHENOXYETHANOL; BUTYLOCTYL SALICYLATE; PYRUS MALUS (APPLE) FRUIT; SHEA BUTTER ETHYL ESTERS; FERRIC OXIDE YELLOW; FERROSOFERRIC OXIDE; SQUALANE; POLYGLYCERYL-4 DIISOSTEARATE/POLYHYDROXYSTEARATE/SEBACATE; CAPRYLIC/CAPRIC TRIGLYCERIDE; TRIDECYL SALICYLATE; WATER; .ALPHA.-BISABOLOL, (+)-; PROPANEDIOL; LECITHIN, SOYBEAN; SODIUM HYDROXIDE; ALKYL (C12-15) BENZOATE; TETRASODIUM GLUTAMATE DIACETATE; SODIUM CHLORIDE

Refy Skin Trio